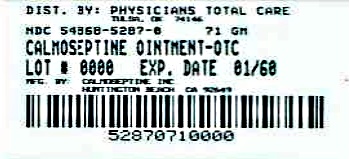 DRUG LABEL: Calmoseptine
NDC: 54868-5287 | Form: OINTMENT
Manufacturer: Physicians Total Care, Inc.
Category: otc | Type: HUMAN OTC DRUG LABEL
Date: 20120601

ACTIVE INGREDIENTS: ZINC OXIDE 20.6 g/113 g; MENTHOL 0.44 g/113 g
INACTIVE INGREDIENTS: FERRIC OXIDE RED; Chlorothymol; Glycerin; Lanolin; Phenol; Sodium Bicarbonate; Thymol

Drug Facts

Active Ingredients

Menthol 0.44%
Zinc Oxide 20.625%

Purpose

External analgesic / Anti-itch
Skin protectant / Anorectal astringent

Uses

Uses: A moisture barrier that prevents and helps heal skin irritation from:
urine, diarrhea, perspiration, fistula damage, feeding tube site leakage,
wound drainage (peri-wound skin), minor burns, cuts, scrapes, itching

Warnings

Warnings: For external use only. Not for deep or puncture wounds. Avoid contact with eyes.

In case of accidental ingestion contact a physician or poison control center immediately. If condition
worsens or does not improve within 7 days, consult a doctor.

Keep out of reach of children

Directions

Directions: Cleanse skin gently with mild skin cleanser. Pat dry or allow to air dry. Apply
a thin layer of Calmoseptine Ointment to reddened or irritated skin 2-4 times daily, or after
each incontinent episode or diaper change to promote comfort and long lasting protection.

Inactive Ingredients

Inactive ingredients: Calamine, chlorothymol, glycerin, lanolin, phenol,
sodium bicarbonate, and thymol in a suitable ointment base

PRINCIPAL DISPLAY PANEL

Calmoseptine Ointment

Menthol 0.44%

Zinc Oxide 20.6%

71 gram tube

NDC 54868-5287-0

Additional barcode labeling by:
Physicians Total Care, Inc.
Tulsa, Oklahoma 74146